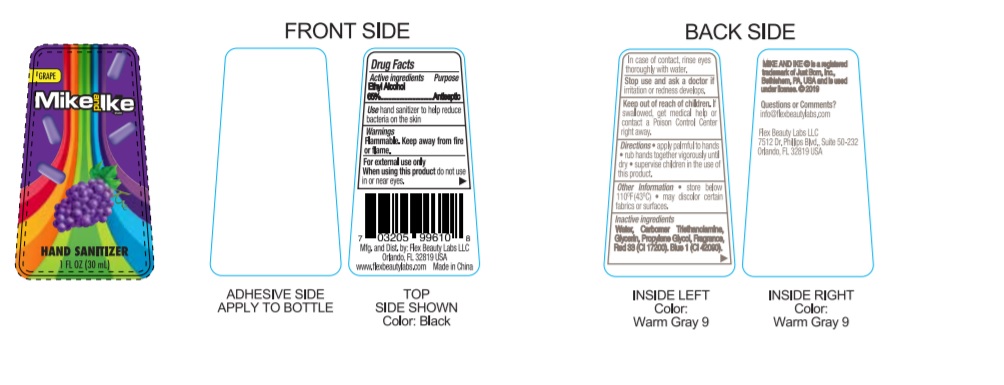 DRUG LABEL: Advanced Hand Sanitizer
NDC: 70939-210 | Form: LIQUID
Manufacturer: Dongguang Shuoguo Silicone Products Co., Ltd.
Category: otc | Type: HUMAN OTC DRUG LABEL
Date: 20191124

ACTIVE INGREDIENTS: ALCOHOL 65 mL/100 mL
INACTIVE INGREDIENTS: CARBOXYPOLYMETHYLENE; GLYCERIN; PROPYLENE GLYCOL; .ALPHA.-TOCOPHEROL ACETATE; TROLAMINE; WATER; D&C RED NO. 33; BASIC BLUE 1; FD&C BLUE NO. 1

Mike & Ike 1 oz Hand Sanitizer: Grape

Drug Facts Active Ingredient

Ethyl Alcohol 65.0%

Purpose

Antiseptic

Uses

Hand Santizer to help reduce bacteria on skin that may cause disease.

Warnings

Flammable. Keep away from heat or flame.

For external use only.

When using this product,

do not use in or near the eyes. In case of contact, rinse eyes thoroughtly with water. Stop use and ask doctor if irritation or rash appears and lasts. Keep out of reach for children.

If swallowed, get medical help or contact a Posion Control Center right away.

Directions:

. Place enough Product in your palm to thoroughtly spread on both hands and rub into the skin until dry.

. Children under 6 years of age should be supervised when using this product.

Other Information:

. Store below 106℉. (41℃)

Inactive Ingredients:

Water (Aqua), Carbomer triethanolamine, Fragrance Red 33, Glycerin, Propylene Glycol, Blue 1